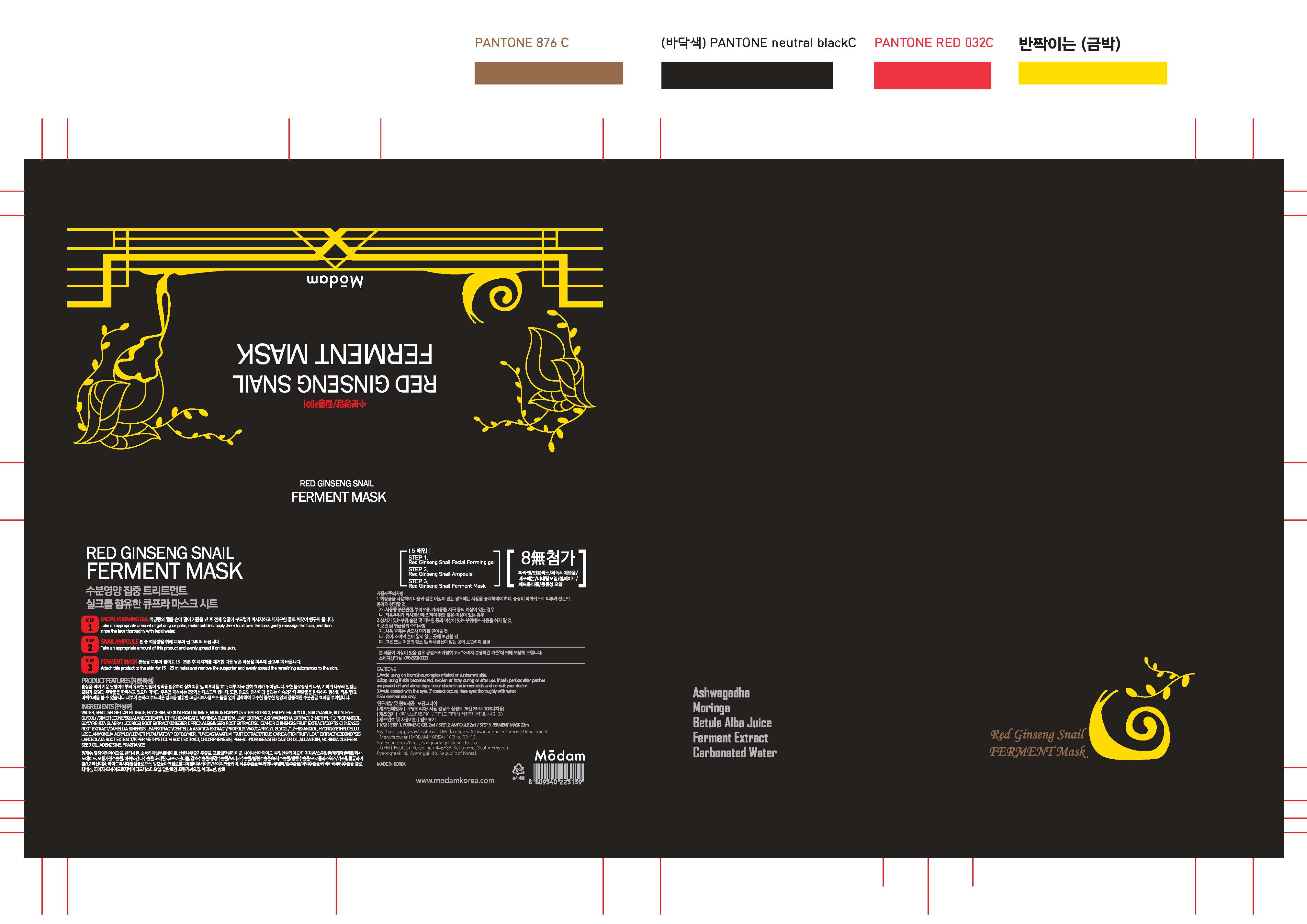 DRUG LABEL: Red Ginseng Snail Ferment Mask
NDC: 72540-003 | Form: LIQUID
Manufacturer: MODAM KOREA
Category: otc | Type: HUMAN OTC DRUG LABEL
Date: 20190508

ACTIVE INGREDIENTS: GLYCERIN 1.131 g/25 mL; Allantoin 0.025 g/25 mL
INACTIVE INGREDIENTS: Water; Butylene Glycol; Niacinamide; Methylpropanediol; Chlorphenesin; Moringa Oleifera Seed Oil; Cetyl Ethylhexanoate; Dimethicone; Phenoxyethanol; Squalane; Propolis Wax; Caprylyl Glycol; 1,2-Hexanediol; PEG-60 Hydrogenated Castor Oil; Ethylhexylglycerin

ACTIVE INGREDIENT

Glycerin (4.525%) - Skin Protectact

Allantoin (0.1%) - Skin Protectact

PURPOSE

Skin Protectact

WARNINGS

Cautions
1. Avoid using on blemishes, pimples, irritated or sunburned skin.
2. Stop using if skin becomes red, swollen or itchy during or after use. If pain persists after patches are peeled off and above signs occur discontinue immediately and consult your doctor.
3. Avoid contact with the eyes. If contact occurs, rinse eyes thoroughly with water.
4. For external use only.

INDICATIONS & USAGE

Step 1. Facial forming gel
Take an appropriate amount of gel on your palm, make bubbles, apply them to all over the face, gently massage the face, and then rinse the face thoroughly with tepid water

Step 2. Snail ampoule
Take an appropriate amount of this product and evenly spread it on the skin.

Step 3. Ferment mask
Attach this product to the skin for 15-25 minutes and remove the supporter and evenly spread the remaining substances to the skin.

DOSAGE & ADMINISTRATION

Step 1. Facial forming gel
Take an appropriate amount of gel on your palm, make bubbles, apply them to all over the face, gently massage the face, and then rinse the face thoroughly with tepid water

Step 2. Snail ampoule
Take an appropriate amount of this product and evenly spread it on the skin.

Step 3. Ferment mask
Attach this product to the skin for 15-25 minutes and remove the supporter and evenly spread the remaining substances to the skin.